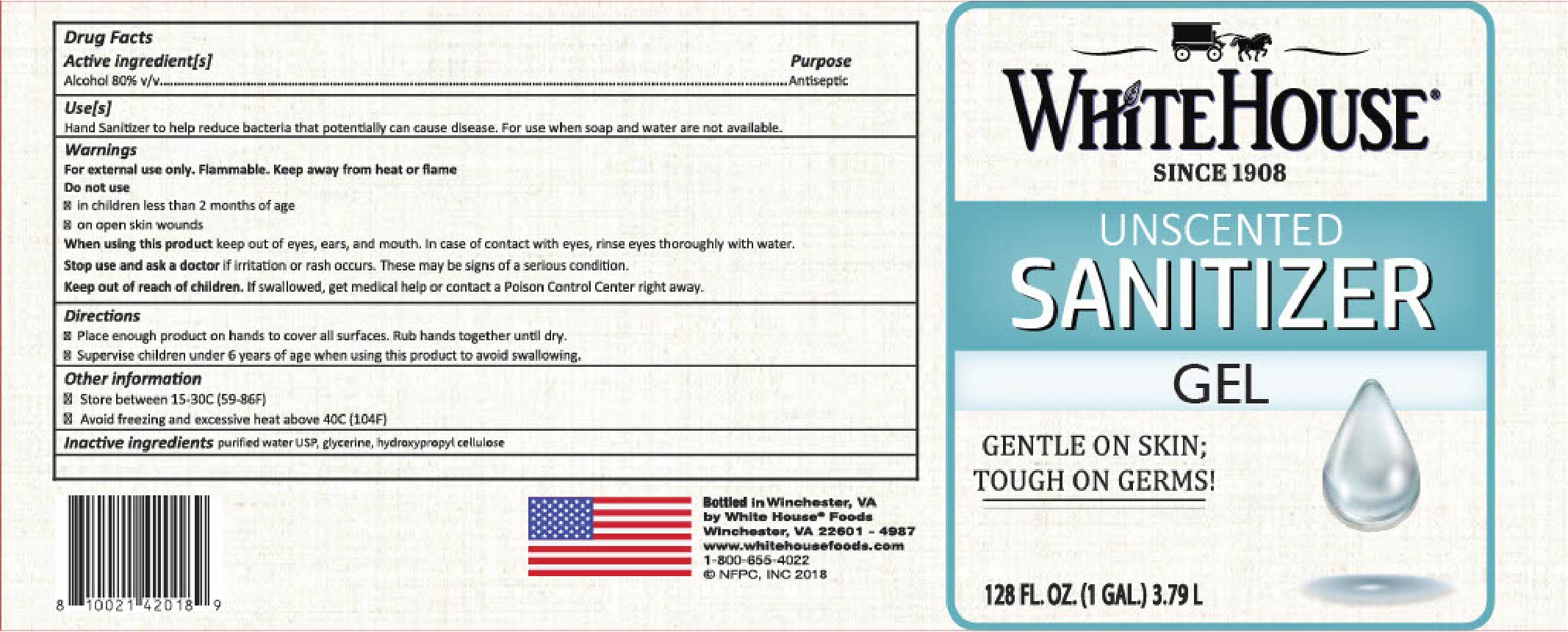 DRUG LABEL: Hand Sanitizer
NDC: 75083-007 | Form: GEL
Manufacturer: National Fruit Product Co.
Category: otc | Type: HUMAN OTC DRUG LABEL
Date: 20201230

ACTIVE INGREDIENTS: ALCOHOL 80 mL/100 mL
INACTIVE INGREDIENTS: GLYCERIN; HYDROXYPROPYL CELLULOSE, UNSPECIFIED; WATER

Active Ingredient(s)

Alcohol 80% v/v. Purpose: Antiseptic

Purpose

Antiseptic, Hand Sanitizer

Use

Hand Sanitizer to help reduce bacteria that potentially can cause disease. For use when soap and water are not available.

Warnings

For external use only. Flammable. Keep away from heat or flame

Do not use

- in children less than 2 months of age
- on open skin wounds

Stop use and ask a doctor if irritation or rash occurs. These may be signs of a serious condition.

Keep out of reach of children. If swallowed, get medical help or contact a Poison Control Center right away.

Directions

- Place enough product on hands to cover all surfaces. Rub hands together until dry.
- Supervise children under 6 years of age when using this product to avoid swallowing.

Other information

- Store between 15-30C (59-86F)
- Avoid freezing and excessive heat above 40C (104F)

Inactive ingredients

water, glycerin,hydroxypropyl cellulose

Package Label - Principal Display Panel

3785 ml NDC 75083-007-28